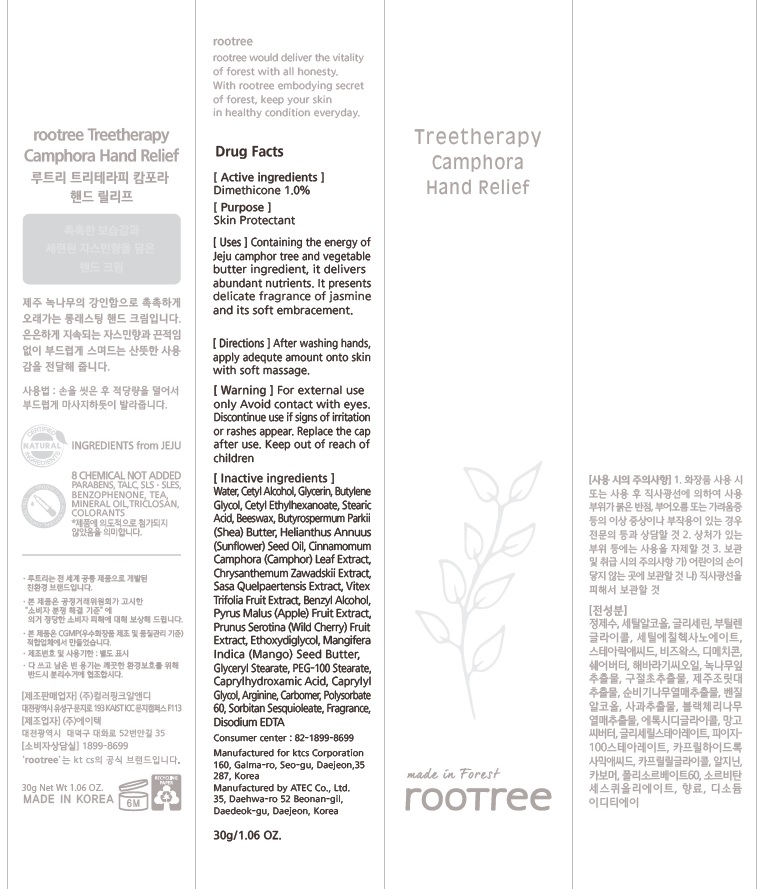 DRUG LABEL: rootree Treetherapy Camphora Hand Relief
NDC: 72441-010 | Form: CREAM
Manufacturer: KTCS Corporation
Category: otc | Type: HUMAN OTC DRUG LABEL
Date: 20180730

ACTIVE INGREDIENTS: Dimethicone 0.3 g/30 g
INACTIVE INGREDIENTS: Water; Cetyl Alcohol

ACTIVE INGREDIENT

Active ingredients: Dimethicone 1.0%

INACTIVE INGREDIENT

Inactive ingredients:

Water,Cetyl Alcohol,Glycerin,Butylene Glycol,Cetyl Ethylhexanoate,Stearic Acid,Beeswax,Butyrospermum Parkii (Shea) Butter,Helianthus Annuus (Sunflower) Seed Oil,Cinnamomum Camphora (Camphor) Leaf Extract,Chrysanthemum Zawadskii Extract,Sasa Quelpaertensis Extract,Vitex Trifolia Fruit Extract,Benzyl Alcohol,Pyrus Malus (Apple) Fruit Extract,Prunus Serotina (Wild Cherry) Fruit Extract,Ethoxydiglycol,Mangifera Indica (Mango) Seed Butter,Glyceryl Stearate,PEG-100 Stearate,Caprylhydroxamic Acid,Caprylyl Glycol,Arginine,Carbomer,Polysorbate 60,Sorbitan Sesquioleate,Fragrance,Disodium EDTA

PURPOSE

Purpose: Skin Protectant

WARNINGS

For external use only.

Avoid contact with eyes.

Discontinue use if signs of irritation or rashes appear.

Replace the cap after use.

Keep out of reach of children

KEEP OUT OF REACH OF CHILDREN

Uses

Containing the energy of Jeju camphor tree and vegetable butter ingredient, it delivers abundant nutrients. It presents delicate fragrance of jasmine and its soft embracement.

Directions

After washing hands, apply adequte amount onto skin with soft massage.